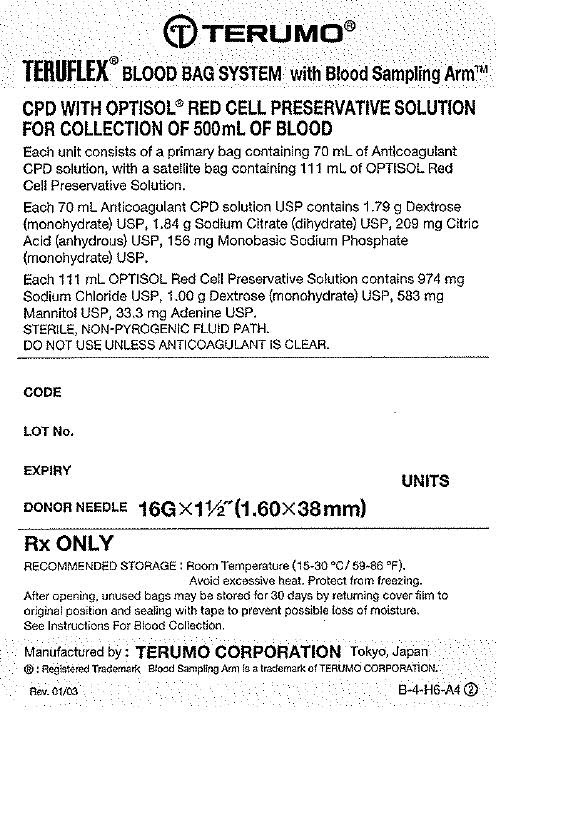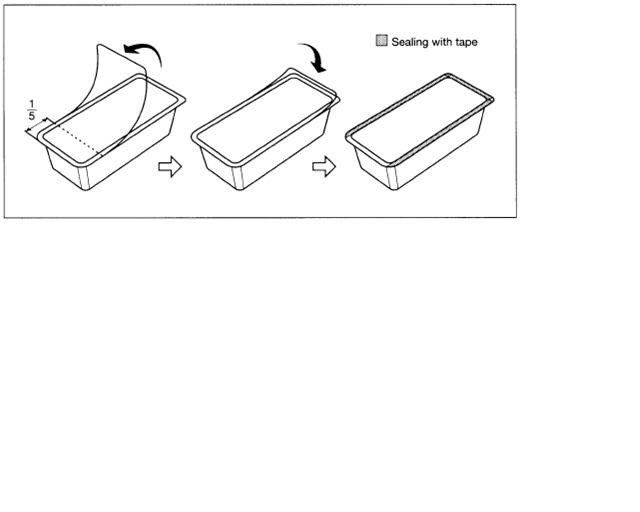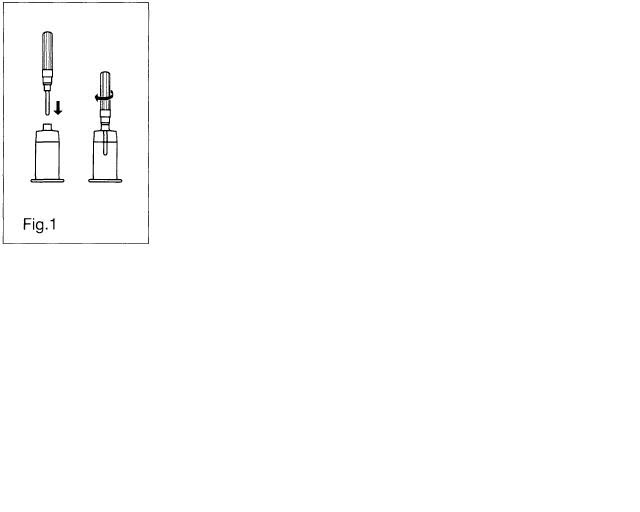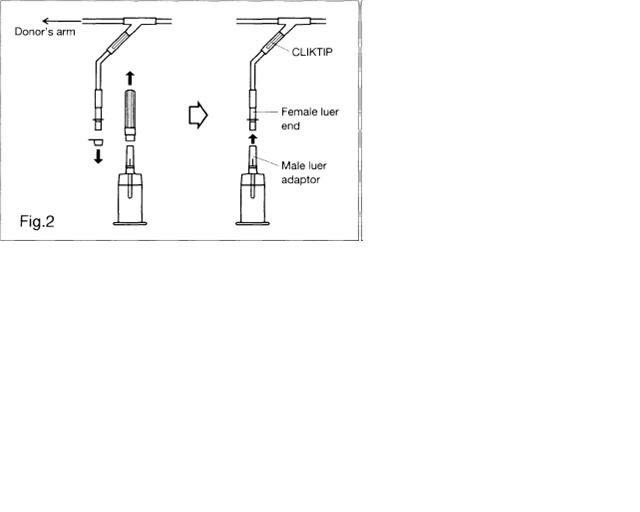 DRUG LABEL: TERUFLEX Blood Bag System with Blood Sampling Arm Anticoagulant Citrate Phosphate Dextrose (CPD) AND OPTISOL (AS-5) Red Cell Preservative
NDC: 53877-009 | Form: KIT | Route: INTRAVENOUS
Manufacturer: Terumo Corporation
Category: prescription | Type: HUMAN PRESCRIPTION DRUG LABEL
Date: 20181207

ACTIVE INGREDIENTS: Trisodium Citrate Dihydrate 26.3 g/1000 mL; SODIUM PHOSPHATE, MONOBASIC, UNSPECIFIED FORM  2.22 g/1000 mL; Dextrose Monohydrate 25.5 g/1000 mL; Anhydrous Citric Acid 2.99 g/1000 mL; Sodium Chloride 877 mg/100 mL; Dextrose Monohydrate 900 mg/100 mL; Mannitol 525 mg/100 mL; Adenine 30 mg/100 mL
INACTIVE INGREDIENTS: Water; Water

TERUFLEX® BLOOD BAG SYSTEM WITH BLOOD SAMPLING ARM® CPD/OPTISOL® SOLUTION

INDICATIONS AND USAGE

Issued 8/96
TERUFLEX® BLOOD BAG SYSTEM With Blood Sampling Arm® CPD/OPTISOL® SOLUTION
Read these instructions carefully before use.
INSTRUCTIONS FOR BLOOD COLLECTION: Use aseptic technique
Materials Needed:
VENOJECT® ll Tube Holder (code P-1316R)
VENOJECT® ll Multi-Sample Luer Adapter (code MN *2000)
VENOJECT® ll Plastic Blood Collection Tubes (or equivalent glass or plastic evacuated blood collection tube)
1. Confirm that all numbered tubing of each blood bag unit contains segment numbers.
2. Make a loose knot in donor tubing below "Y" unless alternate methods are used to seal tubing.
3. Clamp donor tubing.
4. Suspend primary bag as far as possible below the donor's arm.
5. Apply blood pressure cuff or tourniquet to donor's arm. Disinfect site of phlebotomy. If blood pressure cuff is used, inflate cuff to approximately 60 mmHg.
6. Remove needle protector and perform phlebotomy. Remove clamp to permit blood flow into primary bag.
CAUTION Do not touch needle after removing the needle protector.
7. Appropriately secure donor tubing to donor's arm.
8. MIX BLOOD WITH ANTICOAGULANT AT SEVERAL INTERVALS DURING COLLECTION.
9. Collect labeled volume of blood (+/–10%).
10. Tighten knot firmly after collection. Clamp between knot and "Y". Sever donor tubing between the knot and clamp. Alternate methods may be used to seal tubing.
CAUTION Do not use the dielectric tube sealer while the needle is connected to the donor's body.
Anytime before Step #13 below, sever donor tubing between the two seals.
Collect blood samples as follows:
a) Connect VENOJECT II Multi-Sample Luer Adapter to VENOJECT II Tube Holder (Fig. 1).
b) Remove covers and connect multi-sample luer adapter to female luer at end of donor sampling tubing (Fig. 2).
c) Snap CLIKTIP in donor sampling tubing to open blood pathway.
Insert Fig. 1 here

Insert Fig. 2 here

d) Insert blood collection tube (VENOJECT II or equivalent) firmly into VENOJECT II Tube Holder : when full, remove sample tube from holder. Repeat to collect additional samples.
11. Reapply clamp to donor tubing between phlebotomy needle and "Y"; release pressure on donor's arm and remove needle.
CAUTION Discard tubing/phlebotomy needle unit according to institutional procedures.
12. Immediately after collection, invert bag several times to assure blood and anticoagulant are well mixed.
13. Strip blood from the donor tubing into bag, mix well, and allow tubing to refill. Seal on or near X marks on donor tubing to provide numbered aliquots of anticoagulated blood for testing.
14. The time of addition of OPTISOL Solution may vary depending on the processing option selected. Add the solution under one of the following conditions.
a) After removal of plasma from freshly collected blood.
b) Within 8 hours of blood collection if components are prepared.
c) Within 72 hours of collection if blood is refrigerated immediately following collection.
15. Centrifuge the unit to separate red cells from plasma.
16. Snap CLlKTIP (inline closure device) of primary collection bag and transfer plasma into satellite bag. Clamp transfer tubing of satellite bag.
17. Snap CLlKTIP of OPTlSOL Solution bag and drain contents into primary bag containing red blood cells. Seal tubing of primary bag in two places, and cut between seals and separate from satellite bag(s).
NOTE: For TERUFLEX double bags, seal OPTISOL Solution bag tubing in two places and cut between seals. Discard OPTISOL Solution container.
18. Invert the red cell- OPTISOL mixture several times to insure the final AS-5 red cell product is well suspended.
19. Store AS-5 Red Blood Cells between 1-6°C.
20. Infuse AS-5 Red Blood Cells within 42 days of collection.
For further processing, use standard component processing techniques.
To open blister package, peel cover film back four fifths of its length.
After opening, unused bags may be stored for 30 days by returning cover film to original position and sealing with tape to prevent possible loss of moisture.
Insert Fig. 3 here

CAUTIONS
•THE PACKET OF AGELESS CONTAINED IN THIS PACKAGE ABSORBS OXYGEN AND GENERATES HEAT ON REMOVAL AND SHOULD BE HANDLED WITH CARE.
• DISPOSE WITH PACKET IN TRAY.
• DO NOT DISPOSE WITH WASTES CONTAINING VOLATILE OR FLAMMABLE MATERIALS.
• DISCARD AGELESS PACKET WITHOUT OPENING.
TERUMO® TERUMO CORPORATION 44-1, 2-CHOME, HATAGAYA, SHIBUYA-KU, TOKYO, JAPAN
®: Registered Trademark
N-BB-OP-A(SP) 3

Tray/Case Label

TERUFLEX® BLOOD BAG SYSTEM with
BLOOD SAMPLING ARM®
CPD WITH OPTISOL® RED CELL PRESERVATIVE SOLUTION
FOR COLLECTION OF 500mL OF BLOOD
Each unit consists of a collection bag containing 70mL of Anticoagulant
CPD solution, with a satellite bag containing 111mL of OPTlSOL Red
Cell Preservative Solution.
Each 70mL Anticoagulant CPD solution USP contains 1.79g Dextrose
(monohydrate) USP, 1.84g Sodium Citrate (dihydrate) USP, 209mg Citric
Acid (anhydrous) USP, 156mg Monobasic Sodium Phosphate
(monohydrate) USP.
Each 111mL OPTISOL Red Cell Preservative Solution contains 974mg
Sodium Chloride USP, 1.00g Dextrose (monohydrate) USP, 583mg
Mannitol USP, 33.3mg Adenine USP.
STERILE, NON-PYROGENIC FLUID PATH.
DO NOT USE UNLESS ANTICOAGULANT IS CLEAR.
CODE
LOT No.
EXPIRY
UNITS
DONOR NEEDLE 16G x 1 1/2˝ (1.60 x 38mm)
Rx ONLY
RECOMMENDED STORAGE: Room Temperature (15-30°C/59-86°F).
Avoid excessive heat. Protect from freezing.
After opening, unused bags may be stored for 30 days by returning cover film to original
position and sealing with tape to prevent possible loss of moisture.
See Instructions For Blood Collection.
Manufactured by : TERUMO CORPORATION Tokyo, Japan
® : Registered Trademark
Blood Sampling Arm is a trademark of TERUMO CORPORATION.
Rev. 01/03
B-4-H6-A4 2
Place Label here